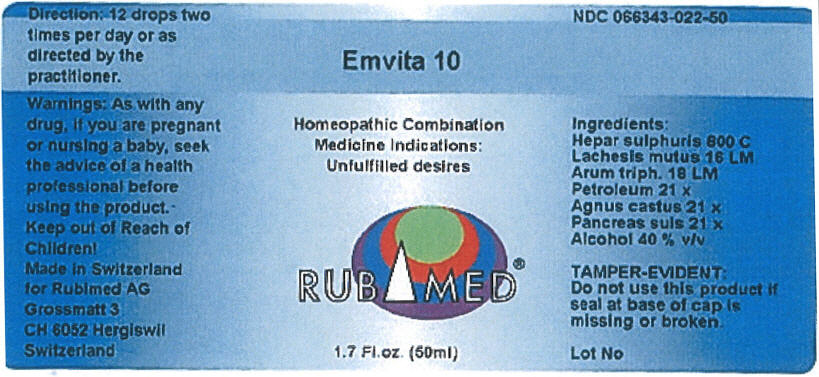 DRUG LABEL: Emvita 10
NDC: 66343-022 | Form: LIQUID
Manufacturer: RUBIMED AG
Category: otc | Type: HUMAN OTC DRUG LABEL
Date: 20150707

ACTIVE INGREDIENTS: CALCIUM SULFIDE 800 [hp_C]/1 mL; LACHESIS MUTA VENOM 16 [hp_M]/1 mL; ARISAEMA TRIPHYLLUM ROOT 18 [hp_M]/1 mL; KEROSENE 21 [hp_X]/1 mL; CHASTE TREE 21 [hp_X]/1 mL; SUS SCROFA PANCREAS 21 [hp_X]/1 mL
INACTIVE INGREDIENTS: ALCOHOL 0.4 mL/1 mL

Emvita 10

INDICATIONS AND USAGE

PURPOSE

Homeopathic Combination Medicine Indications: Unfulfilled desires

Ingredients

INACTIVE INGREDIENT

Hepar sulphuris 800 C
Lachesis mutus 16 LM
Arum triph. 18 LM
Petroleum 21 x
Agnus castus 21 x
Pancreas Suis 21 x
Alcohol 40 % v/v

TAMPER-EVIDENT

Do not use this product if seal at base of cap is missing or broken.

Direction

12 drops two times per day or as directed by the practitioner.

Warnings

PREGNANCY OR BREAST FEEDING

As with any drug, if you are pregnant or nursing a baby, seek the advice of a health professional before using the product.

Keep out of Reach of Children!

PRINCIPAL DISPLAY PANEL - 50 ml Bottle Label

Emvita 10

Homeopathic Combination
Medicine Indications:
Unfulfilled desires

RUBIMED®

1.7 Fl.oz. (50ml)